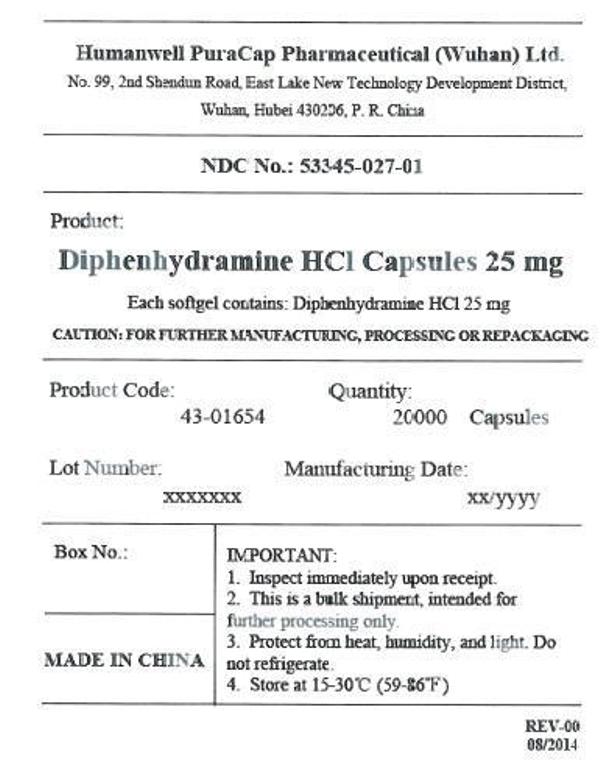 DRUG LABEL: DIPHENHYDRAMINE HYDROCHLORIDE
NDC: 53345-027 | Form: CAPSULE, LIQUID FILLED
Manufacturer: Humanwell PuraCap Pharmaceutical (Wuhan), Ltd.
Category: otc | Type: HUMAN OTC DRUG LABEL
Date: 20241125

ACTIVE INGREDIENTS: DIPHENHYDRAMINE HYDROCHLORIDE 25 mg/1 1
INACTIVE INGREDIENTS: FD&C BLUE NO. 1; FD&C RED NO. 40; GELATIN; GLYCERIN; POLYETHYLENE GLYCOL, UNSPECIFIED; WATER; SORBITOL

DIPHENHYDRAMINE HYDROCHLORIDE capsules, liquid filled

Drug Facts

Active ingredient (in each softgel)

Diphenhydramine HCl 25 mg

Purpose

Nighttime sleep-aid

Uses

- for the relief of occasional sleeplessness
- reduces time to fall asleep if you have difficulty falling asleep

Warnings

Do not use

- for children under 12 years of age
- with any other product containing diphenhydramine, even one used on skin
- with other drugs that cause drowsiness such as antihistamines and nighttime cold/flu products

Ask a doctor before use if you have

- a breathing problem such as asthma, emphysema, or chronic bronchitis
- glaucoma
- difficulty in urination due to enlargement of the prostate gland
- heart disease

Ask a doctor or pharmacist before use if you aretaking sedatives or tranquilizers or any other sleep aid

When using this product

- avoid alcoholic beverages and other drugs that cause drowsiness
- drowsiness will occur
- be careful when driving a motor vehicle or operating machinery

Stop use and ask a doctor ifsleeplessness persists continuously for more than 2 weeks. Insomnia may be a symptom of serious underlying medical illness.

PREGNANCY OR BREAST FEEDING

If pregnant or breast-feeding,ask a health professional before use.

Keep out of reach of children. Overdose warning:Taking more than directed can cause serious health problems. In case of overdose, get medical help or contact a Poison Control Center right away.

Directions

- take only one dose per day (24 hours) - see Overdose warning

adults & children

12 yrs of age & over

ONE dose = TWO 25 mg softgels (50 mg)

at bedtime if needed or as directed by a doctor

Other information

- store at 15°-30°C (59°-86°F)
- avoid excessive heat above 40°C (104°F) and high humidity
- protect from light

Inactive ingredients

FD&C blue #1, FD&C red #40, gelatin, glycerin, polyethylene glycol, purified water, sorbitol special and white edible ink

Manufactured by:
Humanwell PuraCap Pharmaceutical (Wuhan) Ltd.
Wuhan, Hubei 430206,
China

PRINCIPAL DISPLAY PANEL - Shipping Label

DIPHENHYDRAMINE HYDROCHLORIDE CAPSULES, 25 mg

Quantity : 20000 Capsules
NDC. No : 53345-027-01

IMPORTANT:

Inspect immediately upon receipt.
This is a bulk shipment, intended for further processing only.
Protect from heat, humidity, and light. Do not refrigerate.
Store at 15-30°C (59-86°F)
CAUTION : "FOR FURTHER MANUFACTURING, PROCESSING OR REPACKAGING"